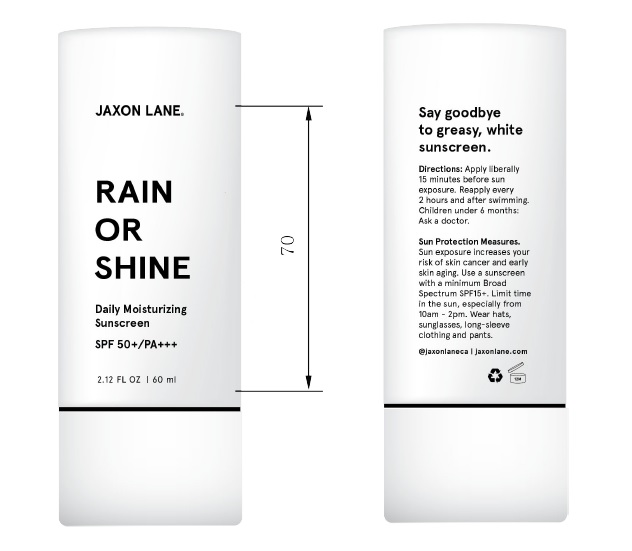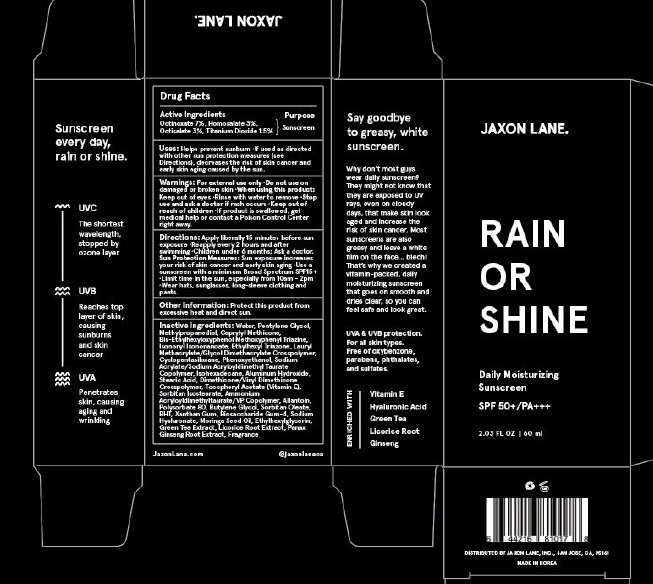 DRUG LABEL: RAIN OR SHINE
NDC: 73072-002 | Form: CREAM
Manufacturer: Jaxon Lane, Inc.
Category: otc | Type: HUMAN OTC DRUG LABEL
Date: 20201019

ACTIVE INGREDIENTS: OCTINOXATE 7 g/100 mL; HOMOSALATE 3 g/100 mL; OCTISALATE 3 g/100 mL; TITANIUM DIOXIDE 1.5 g/100 mL
INACTIVE INGREDIENTS: WATER; PENTYLENE GLYCOL; METHYLPROPANEDIOL; CAPRYLYL TRISILOXANE; BEMOTRIZINOL; ISONONYL ISONONANOATE; ETHYLHEXYL TRIAZONE; LAURYL METHACRYLATE/GLYCOL DIMETHACRYLATE CROSSPOLYMER; CYCLOMETHICONE 5; PHENOXYETHANOL; SODIUM ACRYLATE/SODIUM ACRYLOYLDIMETHYLTAURATE COPOLYMER (4000000 MW); ISOHEXADECANE; ALUMINUM HYDROXIDE; STEARIC ACID; DIMETHICONE/VINYL DIMETHICONE CROSSPOLYMER (SOFT PARTICLE); .ALPHA.-TOCOPHEROL ACETATE; SORBITAN ISOSTEARATE; AMMONIUM ACRYLOYLDIMETHYLTAURATE/VP COPOLYMER; ALLANTOIN; POLYSORBATE 80; BUTYLENE GLYCOL; SORBITAN MONOOLEATE; BUTYLATED HYDROXYTOLUENE; XANTHAN GUM; BIOSACCHARIDE GUM-4; HYALURONATE SODIUM; MORINGA OLEIFERA SEED OIL; ETHYLHEXYLGLYCERIN; GREEN TEA LEAF; GLYCYRRHIZA GLABRA; ASIAN GINSENG

RAIN OR SHINE

Active ingredients

Octinoxate, Homosalate, Octisalate, titanium dioxide

Purpose: Sunscreen

Inactive Ingredients

Water, Pentylene Glycol, Methylpropanediol, Caprylyl Methicone, Bis-Ethylhexyloxyphenol Methoxyphenyl Triazine, Isononyl Isononanoate, Ethylhexyl Triazone, Lauryl Methacrylate/Glycol Dimethacrylate Crosspolymer, Cyclopentasiloxane, Phenoxyethanol, Sodium Acrylate/Sodium Acryloyldimethyl Taurate Copolymer, Isohexadecane, Aluminium Hydroxide, Stearic Acid, Dimethicone/Vinyl Dimethicone Crosspolymer, Tocopheryl Acetate (Vitamin E), Sorbitan Isostearate, Ammoniumacryloyldimethyl Taurate/VP Copolymer, Allantoin, Polysorbate 80, Butylene Glycol, Sorbitan Oleate, BHT Xanthan Gum, Biosaccharide Gum-4, Sodium Hyaluronate, Moringa Seed Oil, Ethylhexylglycerin, Green Tea Extract, Licorice Root Extract, Panax Ginseng Root Extract, Fragrance

Uses:

Helps prevent sunburn. If used as directed with other sun protection measures (see Directions) decreases the risk of skin cancer and early skin aging caused by the sun.

Warnings:

For external use only. Do not use on damaged or broken skin. When using this product: Keep out of eyes. Rinse with water to remove. Stop use and ask a doctor if rash occurs. Keep out of reach of children. If product is swallowed, get medical help or contact a Poison Control Center right away.

Directions:

Apply liberally 15 minutes before sun exposure. Reapply every 2 hours and after swimming. Children under 6 months: Ask a doctor.

Sun Protection Measures: Sun exposure increases your risc of skin cancer and early skin aging. Use a sunscreen with a minium Broad Spectrum SPF15+ Limit time in the Sun, especially from 10 am - 2pm, wear hats, sunglasses, long-sleeve, clothing and pants.

Other Information:

Protect this product from excessive heat and direct sun.